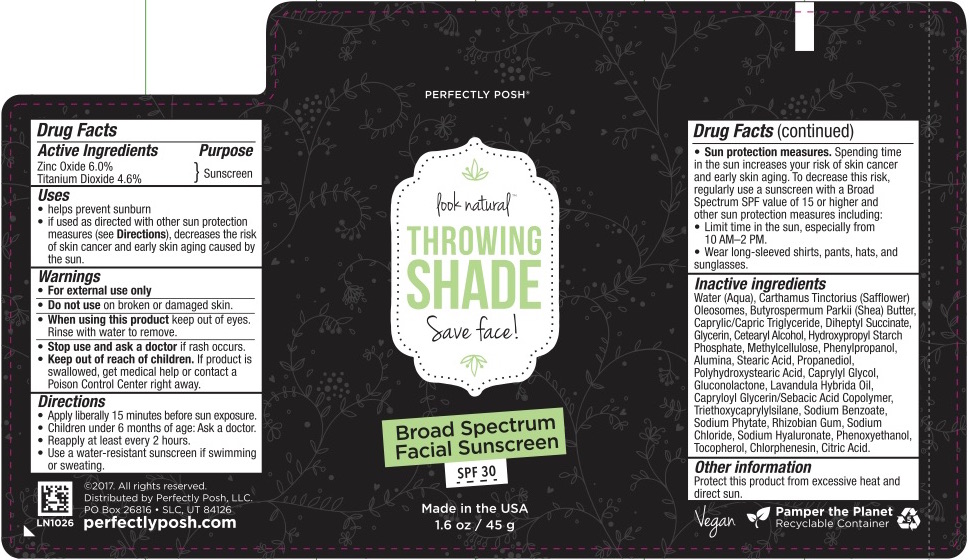 DRUG LABEL: Perfectly Posh THROWING SHADE SPF30 Broad Spectrum Facial Sunscreen
NDC: 71140-0332 | Form: CREAM
Manufacturer: Perfectly Posh, LLC
Category: otc | Type: HUMAN OTC DRUG LABEL
Date: 20170215

ACTIVE INGREDIENTS: ZINC OXIDE 6 g/100 g; TITANIUM DIOXIDE 4.6 g/100 g
INACTIVE INGREDIENTS: ALUMINUM OXIDE; SHEA BUTTER; GLYCERIN; PHENYLPROPANOL; CHLORPHENESIN; ANHYDROUS CITRIC ACID; SODIUM CHLORIDE; DIHEPTYL SUCCINATE; HYALURONATE SODIUM; PHENOXYETHANOL; CETYL ALCOHOL; LAVENDER OIL; TRIETHOXYCAPRYLYLSILANE; SODIUM BENZOATE; POLYHYDROXYSTEARIC ACID (2300 MW); TOCOPHEROL; STEARIC ACID D7; PROPANEDIOL; HYDROXYPROPYL DISTARCH PHOSPHATE, HIGH AMYLOSE CORN; WATER; CAPRYLYL GLYCOL; GLUCONOLACTONE; CARTHAMUS TINCTORIUS (SAFFLOWER) OLEOSOMES; METHYLCELLULOSE (15 CPS); GLYCERYL CAPRYLATE/CAPRATE; PHYTATE SODIUM; CAPRYLOYL GLYCERIN/SEBACIC ACID COPOLYMER (2000 MPA.S); RHIZOBIAN GUM

Perfectly Posh THROWING SHADE SPF30 Broad Spectrum Facial Sunscreen

Drug Facts

Active Ingredient

Zinc Oxide 6%

Titanium Dioxide 4.6%

Purpose

Sunscreen

Uses

- Helps prevent sunburn
- If used as directed with other sun protection measures (see Directions), decreases the risk of skin cancer and early skin aging caused by the sun.

Warnings

For external use only

Do not use on damaged or broken skin. Stop use and ask a doctor if rash occurs.

When using this product keep out of eyes. Rinse with water to remove.

Keep out of reach of children. If product is swallowed, get medical help or contact a Poison Control Center right away.

Directions

- Apply liberally 15 minutes before sun exposure.
- Children under 6 months of age: ask a doctor.
- Reapply at least every 2 hours.
- Use a water-resistant sunscreen if swimming or sweating.

Sun Protection Measures:

- Spending time in the sun increases your risk of skin cancer and early skin aging.
- To decrease this risk, regularly use a sunscreen with a Broad Spectrum SPF value of 15 or higher and other sun protection measures including:
  - Limit time in the sun, especially from 10am-2pm.
  - Wear long-sleeved shirts, pants, hats, and sunglasses.

Inactive Ingredients

Water (Aqua), Carthamus Tinctorius (Safflower) Oleosomes, Butyrospermum Parkii (Shea) Butter, Caprylic/Capric Triglyceride, Diheptyl Succinate, Glycerin, Cetearyl Alcohol, Hydroxypropyl Starch Phosphate, Methylcellulose, Phenylpropanol, Alumina, Stearic Acid, Propanediol, Polyhydroxystearic Acid, Caprylyl Glycol, Gluconolactone, Lavandula Hybrida Oil, Capryloyl Glycerin/Sebacic Acid Copolymer, Triethoxycaprylylsilane, Sodium Benzoate, Sodium Phytate, Rhizobian Gum, Sodium Chloride, Sodium Hyaluronate, Phenoxyethanol, Tocopherol, Chlorphenesin, Citric Acid.

Other Information

Protect this product from excessive heat and sun.

PRINCIPAL DISPLAY PANEL

Broad Spectrum

Facial Sunscreen

SPF 30

1.6 oz/45 g